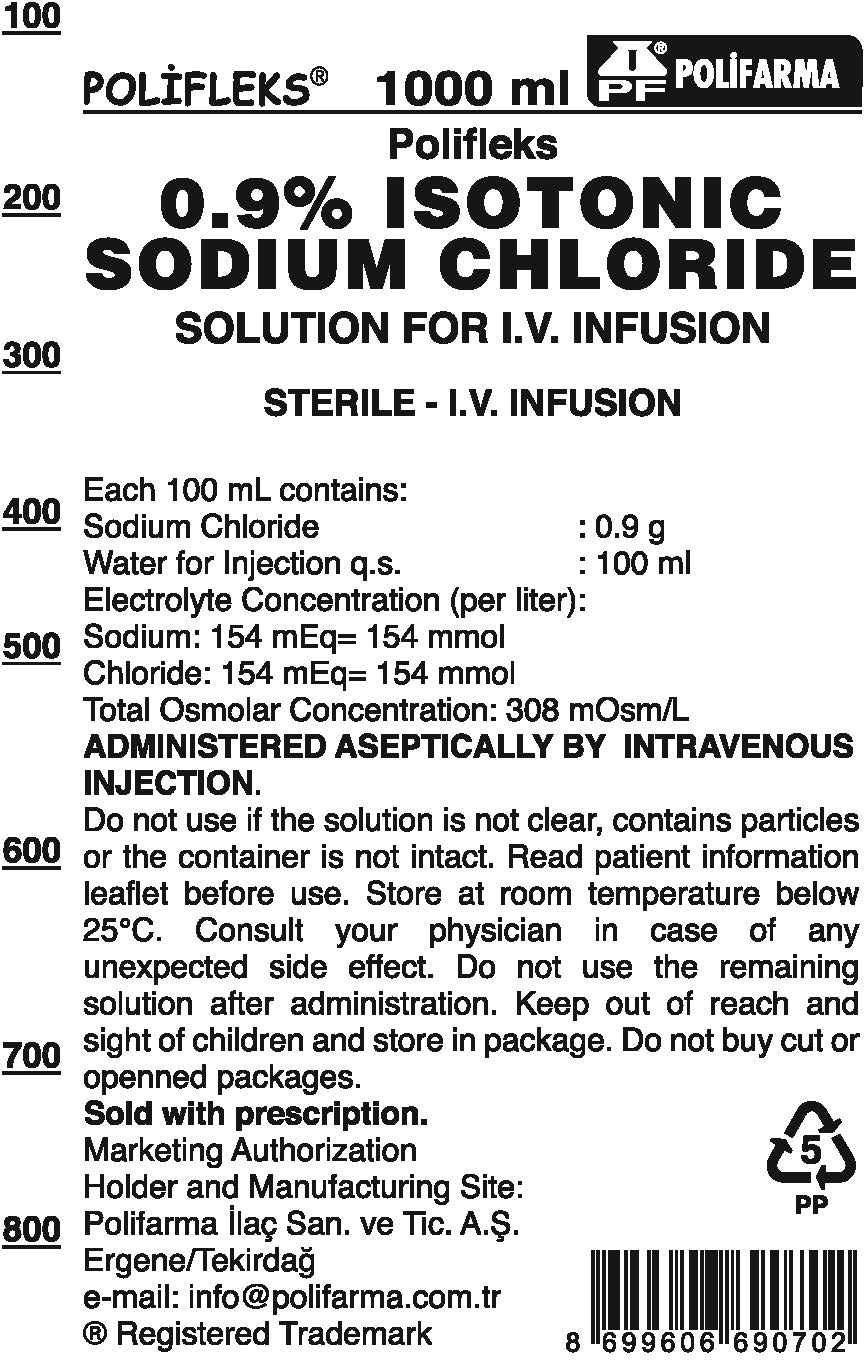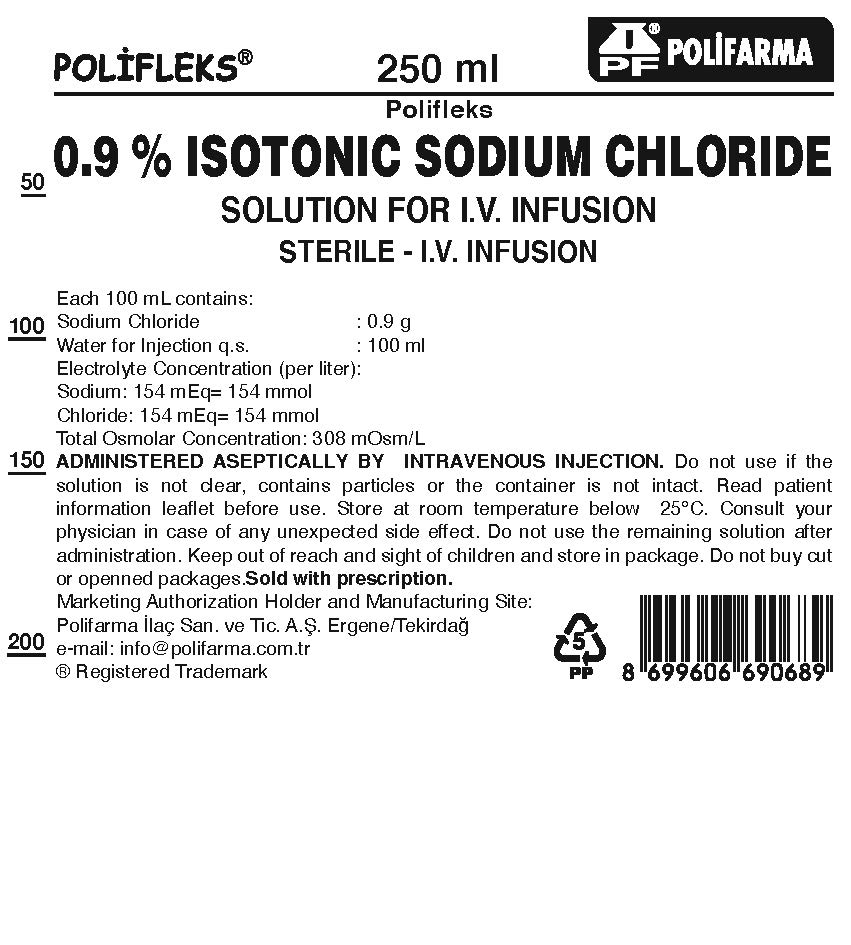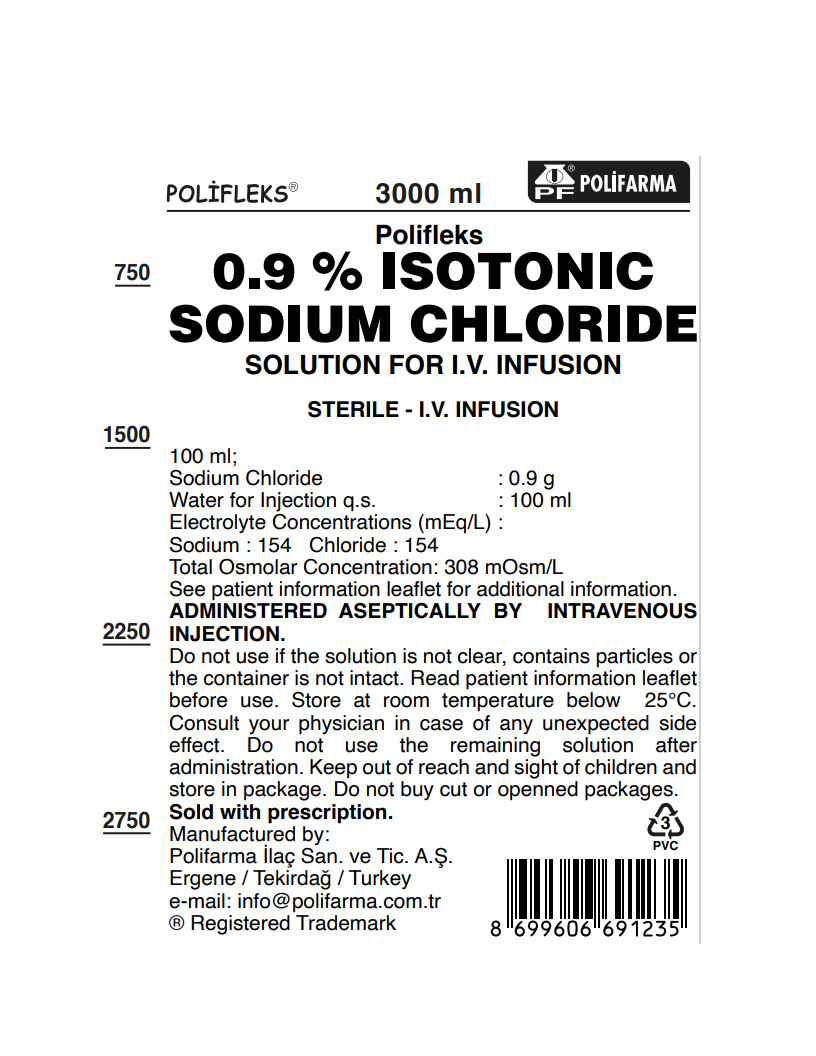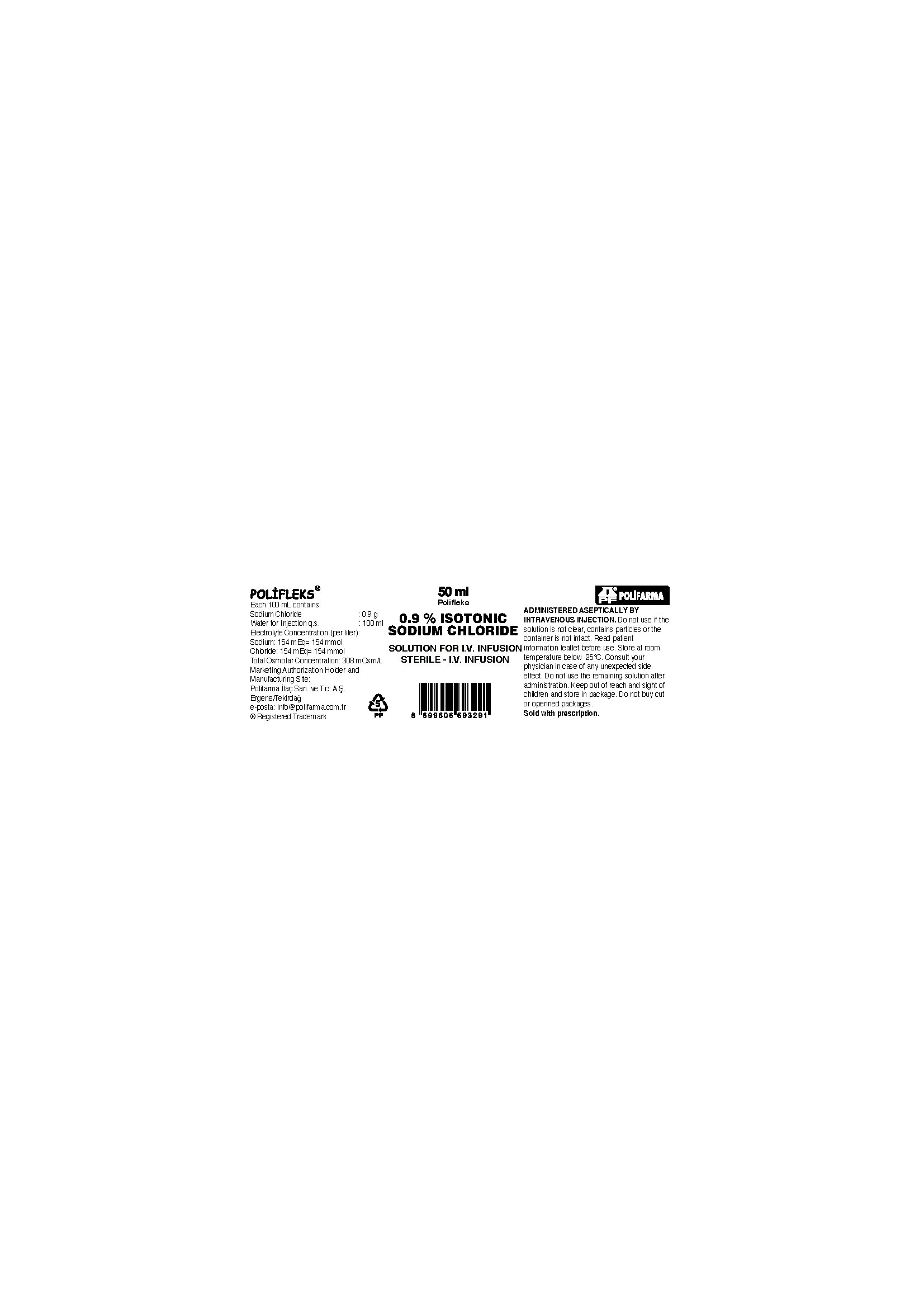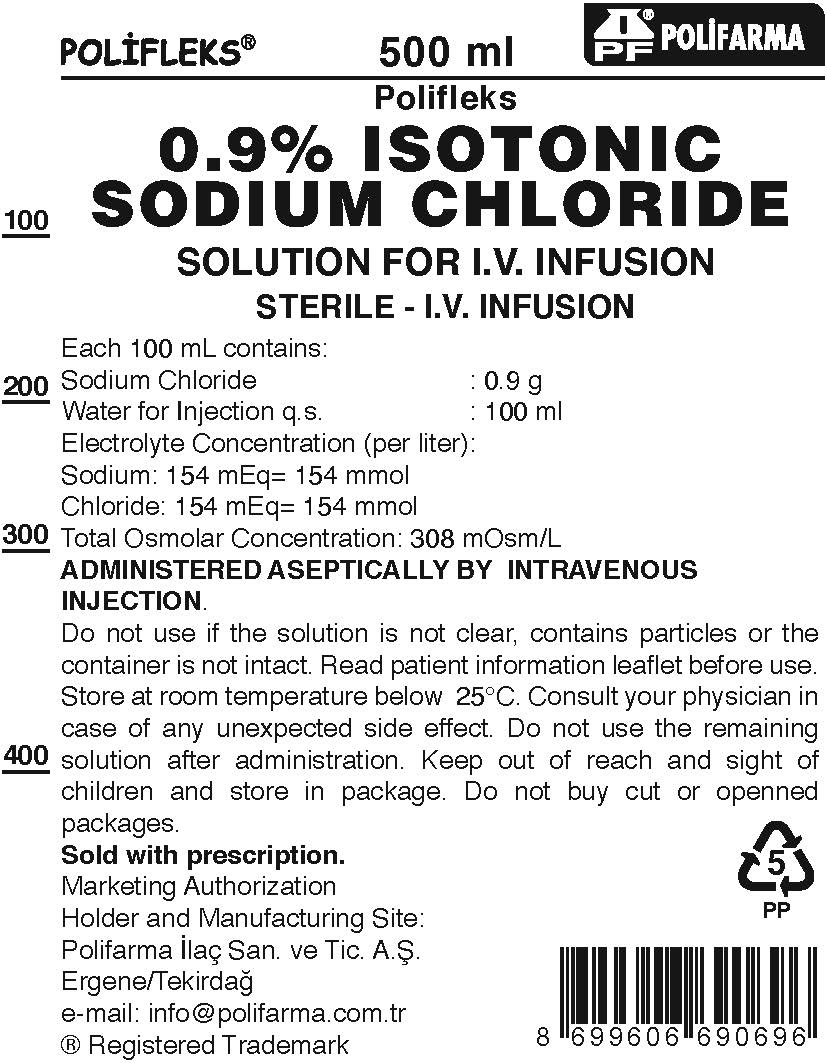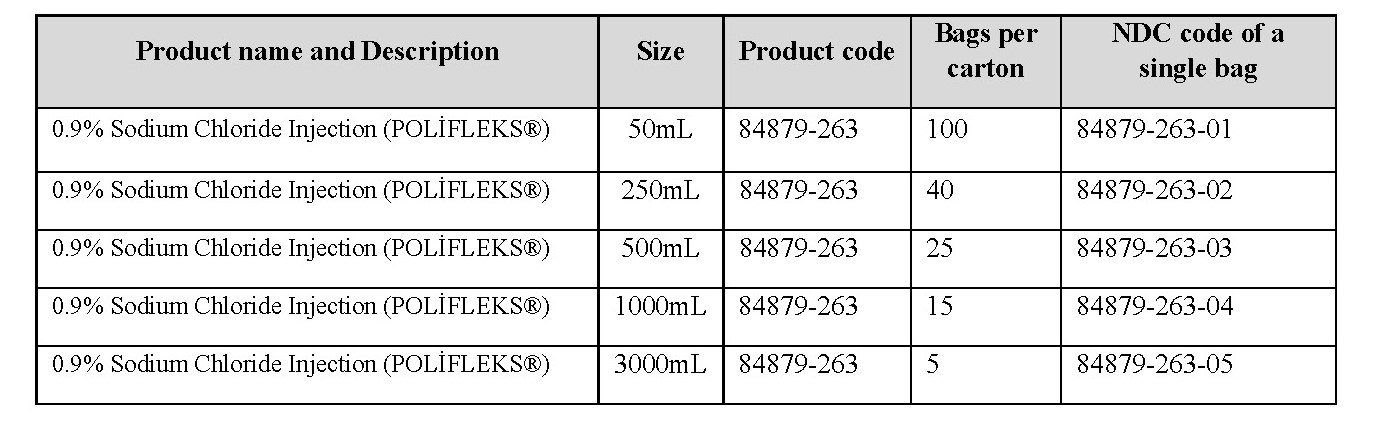 DRUG LABEL: Polifleks
NDC: 84879-263 | Form: SOLUTION
Manufacturer: POLIFARMA ILAC SANAYI VE TICARET ANONIM SIRKETI CORLU SUBESI
Category: prescription | Type: HUMAN PRESCRIPTION DRUG LABEL
Date: 20250615

ACTIVE INGREDIENTS: ISOTONIC SODIUM CHLORIDE SOLUTION 0.9 g/100 mL

HEALTH CARE PROVIDER LETTER

[Text Box: Subject: Temporary Importation of 0.9% Sodium Chloride Injection Products from Turkey to address drug shortages.] February 21, 2025

Dear Healthcare Provider,

In order to address shortages of Sodium Chloride Injection, USP, in the United States, GLOBAL GUARD INC. is coordinating with the U.S. Food and Drug Administration (FDA) to temporarily import 0.9% Sodium Chloride Solution from POLIFARMA’s manufacturing facility in Turkey.

FDA has not approved these products manufactured by Polifarma.

You may be provided with additional letters for other imported products you receive. Please read each letter in its entirety because as each letter may contain different product-specific information.

At this time, no other entity except Global Guard, Inc is authorized by the FDA to import or to distribute this Polifarma product in the United States.

Effective immediately, and during this temporary period, Global Guard, Inc., will offer the following presentations of Polifarma POLİFLEKS® 0.9% Isotonic Sodium Chloride Solution:

It is important to note the following:

The imported products do not have a UPC barcode on the bag, rather they have a GTIN barcode that contains the product Global Trade Identification Number (GTIN). The barcode on the imported product labels may not register accurately in U.S. scanning systems. Alternative procedures should be followed to ensure that the correct drug product is being used in all systems and processes and administered to individual patients. For example, institutions should consider manually inputting the product into their systems and ensure that barcode systems provide correct information when the product is scanned.

These products are available only by prescription in the U.S. the imported products do not have the statement “Rx only” they state Sold with Prescription on the labeling.

After opening the carton or box, the bags should be inspected visually to confirm there is no visible particulate matter or bag defects; such as, leaks. Container integrity is imperative to ensure sterility of products listed in Table 1. Parenteral drug products should be inspected visually for particulate matter and bag defects prior to administrations, whenever solution or container permits. This requirement is specifically stated on the package for the products which are subject to this notification.
You should perform a visual inspection of the bag prior to administration of the solution.
USE A NEW BAG IF PARTICULATES ARE VISIBLE OR IF THE IV BAG CONTAINS A LEAK

Additional key differences in the labeling between the FDA-approved products and the imported products are stated in the product comparison tables at the end of this letter as follows:

Table 1. Key differences between FDA-approved and imported 0.9% Sodium Chloride Injection USP

Table 2. Label images of FDA-approved and imported 0.9% Sodium Chloride Injection USP

Please refer to FDA-approved prescribing information as follows:

0.9% Sodium Chloride Injection, USP, Polifleks Polypropylene I.V. bag (click here)

Reporting Adverse Events:

Healthcare providers should report adverse events associated with the use of POLİFLEKS 0.9% Isotonic Sodium Chloride Solution for I.V. Infusion to GLOBAL GUARD LLC by phone: 1-800-555-1212 NEED TO ESTABLISH # ; email: AER@GLOBALGUARDCORP.COM NEED TO ESTABLISH

Adverse reactions or quality problems experienced with the use of this product may be reported to the FDA’s MedWatch Adverse Event Reporting program either online, by regular mail or by fax:

Complete and submit the report Online: www.fda.gov/medwatch/report.htm
Regular Mail or Fax: Download form https://www.accessdata.fda.gov/scripts/medwatch/index.cfm or call 1-800-332-1088 to request a reporting form, then complete and return to the address on the pre-addressed form or submit by fax to 1-800-FDA-0178 (1-800-332-0178).

Please ensure that your staff and others in your institution who may be involved in the administration of POLİFLEKS 0.9% Isotonic Sodium Chloride Solution for I.V. Infusion receives a copy of this letter and reviews the information.

To place an order:

please contact GLOBAL GUARD LLC at orders@globalguardcorp.com

For all other inquiries please contact GLOBAL GUARD LLC at 1-800-555-1212 (phone); email: INFO@GLOBALGUARDCORP.COM

Gürmen Kaynar Michael Bogdan

International Markets and President
Business Development Director Global Guard LLC
POLIFARMA İLAC SAN. ve TIC. A.Ş.

Table 1. Key differences between FDA-approved and imported 0.9% Sodium Chloride Injection USP

FDA approved product

Imported product from Turkey

Product name

Sodium Chloride Injection, USP

in VIAFLEX Plastic Container

POLİFLEKS 0.9% Isotonic Sodium Chloride Solution for I.V. Infusion

Label volume

1,000 mL

1,000 mL

Language of the labels

English

English

Indications

Sodium Chloride Injection, USP is indicated as a source of water and electrolytes. 0.9% Sodium Chloride Injection, USP is also indicated for use as a priming solution in hemodialysis procedures.

POLİFLEKS 0.9% ISOTONIC SODIUM CHLORIDE is indicated in the following situations:

- Treatment of isotonic extracellular dehydration

- Treatment of sodium depletion

- As diluent of compatible drugs for parenteral administration.

Active Ingredients

Each 100 ml contains 900 mg Sodium Chloride, USP

Each 100 ml contains 900 mg Sodium Chloride

Additional Information

pH is 5.0 (4.5 to 7.0) Osmolarity 308 mOsm/L (calc)

pH is 5.5 (4.5 – 7.0). Osmolarity of solution is 308 mOsmol/l.

Storage conditions

Store at room temperature 25 ° C/77° F.

Store at room temperature below 25°C.

Container type

VIAFLEX PVC

POLIFLEKS POLYPROPYLENE

Medication and administration port closures

Contains medication port and administration port; Pull off port protector (blue color), right side

Contains medication port and administration port; Pull off port protector (CLEAR/no color), right side

[A close-up of a plastic tube Description generated with high confidence]

Table 2. Label images of FDA-approved and imported 0.9% Sodium Chloride Injections

FDA approved product

Imported product from Turkey

0.9% Sodium Chloride Injection USP

0.9% ISOTONIC SODIUM CHLORIDE SOLUTION

Label Color: Black barcode not shown

1,000 mL shown as representative label

Label: Color Black barcode shown 1000 mL shown as representative label